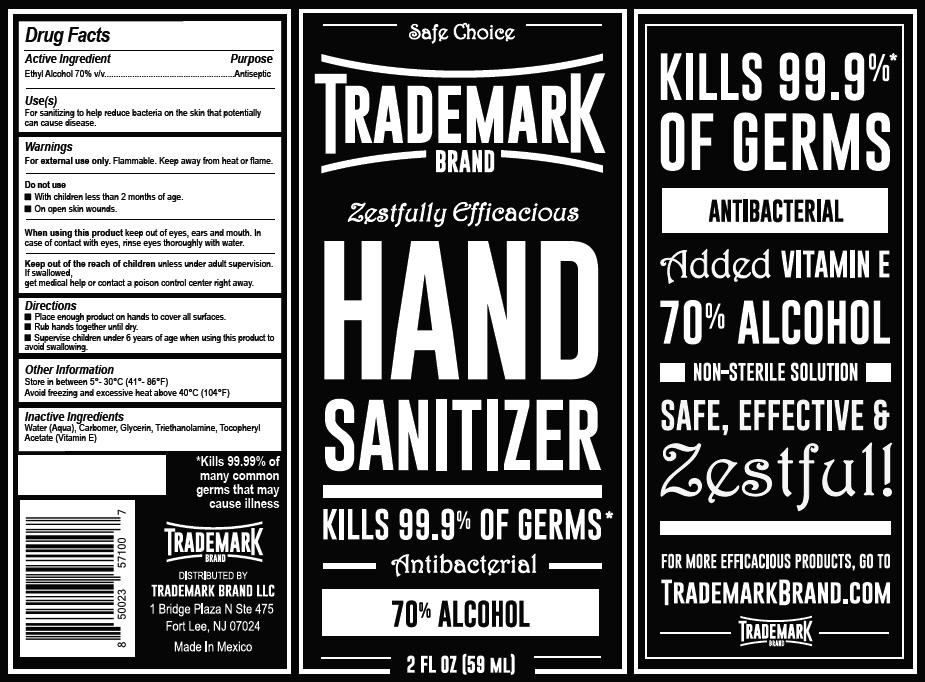 DRUG LABEL: Hand Sanitizer
NDC: 79882-001 | Form: GEL
Manufacturer: Solve Together, LLC
Category: otc | Type: HUMAN OTC DRUG LABEL
Date: 20201203

ACTIVE INGREDIENTS: Alcohol 70 mL/100 mL
INACTIVE INGREDIENTS: WATER; CARBOMER HOMOPOLYMER, UNSPECIFIED TYPE; GLYCERIN; TROLAMINE; .ALPHA.-TOCOPHEROL

Hand Sanitizer

Drug Facts

Active Ingredient

Ethyl Alcohol 70% v/v

Purpose

Antiseptic

Use(s)

For sanitizing to help reduce bacteria on the skin that potentially can cause disease.

Warnings

For external use only. Flammable. Keep away from heat or flame.

Do not use

- With children less than 2 months of age.
- On open skin wounds.

When using this product keep out of eyes, ears and mouth. In case of contact with eyes, rinse eyes thoroughly with water.

KEEP OUT OF REACH OF CHILDREN

Keep out of the reach of children unless under adult supervision. If swallowed, get medical help or contact a poison control center right away.

Directions

- Place enough product on hands to cover all surfaces.
- Rub hands together until dry.
- Supervise children under 6 years of age when using this product to avoid swallowing.

Other Information

Store in between 5°-30°C (41°-86°F)

Avoid freezing and excessive heat above 40°C (104°F)

Inactive Ingredients

Water (Aqua), Carbomer, Glycerin, Triethanolamine, Tocopheryl Acetate (Vitamin E)

DISTRIBUTED BY
TRADEMARK BRAND LLC
1 Bridge Plaza N Ste 475
Fort Lee, NJ 07024

PRINCIPAL DISPLAY PANEL - 59 ML Bottle Label

Safe Choice

TRADEMARK
BRAND

Zestfully Efficacious
HAND
SANITIZER

KILLS 99.9% OF GERMS*

Antibacterial

70% ALCOHOL

2 FL OZ (59 ML)